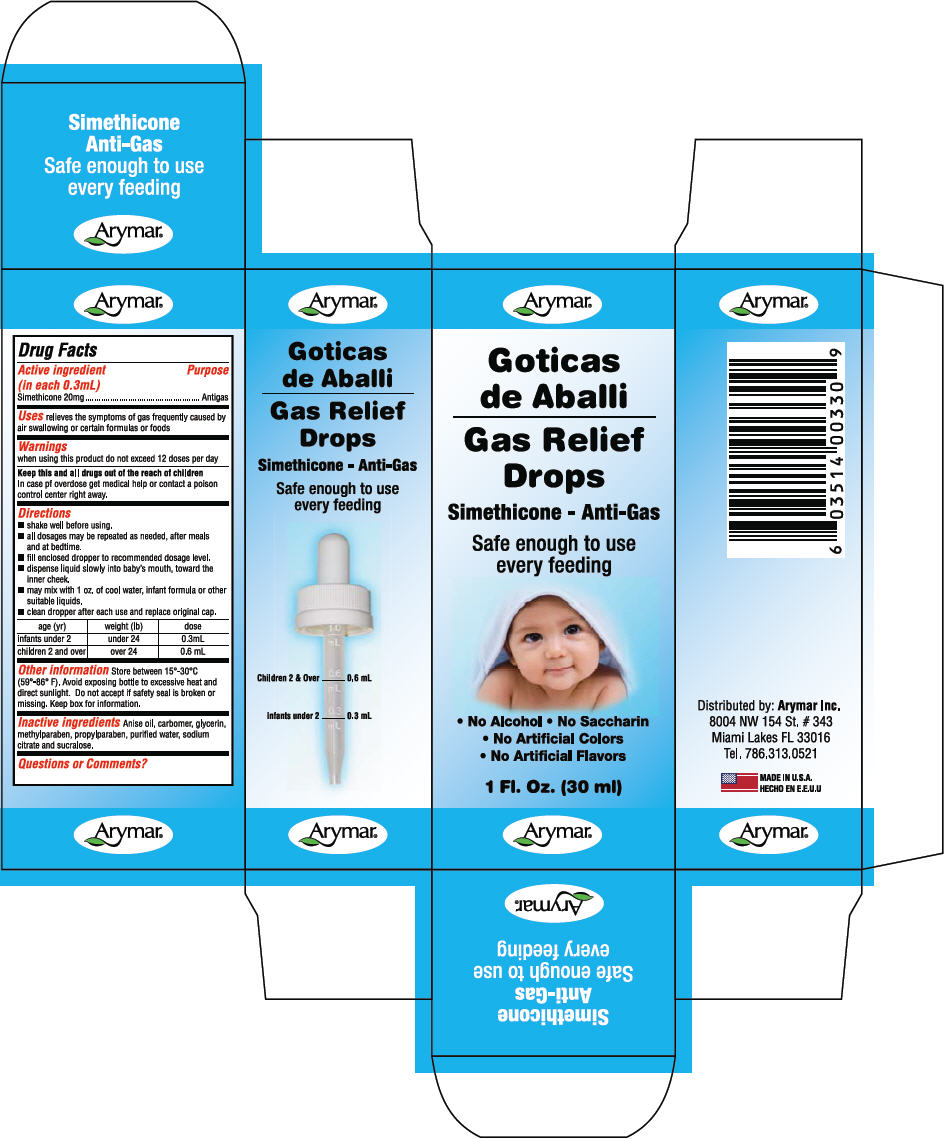 DRUG LABEL: Gas Relief Drops
NDC: 70570-0197 | Form: LIQUID
Manufacturer: Arymar Inc.
Category: otc | Type: HUMAN OTC DRUG LABEL
Date: 20190304

ACTIVE INGREDIENTS: Dimethicone 20 mg/0.3 mL
INACTIVE INGREDIENTS: Anise Oil; Carboxypolymethylene; Glycerin; Methylparaben; Propylparaben; Water; Sodium Citrate, Unspecified Form; Sucralose

Gas Relief Drops

Drug Facts

Active ingredient (in each 0.3mL)

Simethicone 20mg

Purpose

Antigas

Uses

relieves the symptoms of gas frequently caused by air swallowing or certain formulas or foods

Warnings

when using this product do not exceed 12 doses per day

KEEP OUT OF REACH OF CHILDREN

Keep this and all drugs out of the reach of children

In case pf overdose get medical help or contact a poison control center right away.

Directions

- shake well before using.
- all dosages may be repeated as needed, after meals and at bedtime.
- fill enclosed dropper to recommended dosage level.
- dispense liquid slowly into baby's mouth, toward the inner cheek.
- may mix with 1 oz. of cool water, infant formula or other suitable liquids.
- clean dropper after each use and replace original cap.

age (yr) | weight (lb) | dose
infants under 2 | under 24 | 0.3mL
children 2 and over | over 24 | 0.6 mL

Other information

Store between 15°-30°C (59°-86° F). Avoid exposing bottle to excessive heat and direct sunlight. Do not accept if safety seal is broken or missing. Keep box for information.

Inactive ingredients

Anise oil, carbomer, glycerin, methylparaben, propylparaben, purified water, sodium citrate and sucralose.

Distributed by: Arymar Inc.
8004 NW 154 St. # 343
Miami Lakes FL 33016

PRINCIPAL DISPLAY PANEL - 30 ml Bottle Carton

Arymar®

Gas Relief
Drops

Simethicone - Anti-Gas

Safe enough to use
every feeding

● No Alcohol ● No Saccharin
● No Artificial Colors
● No Artificial Flavors

1 Fl. Oz. (30 ml)

Arymar®